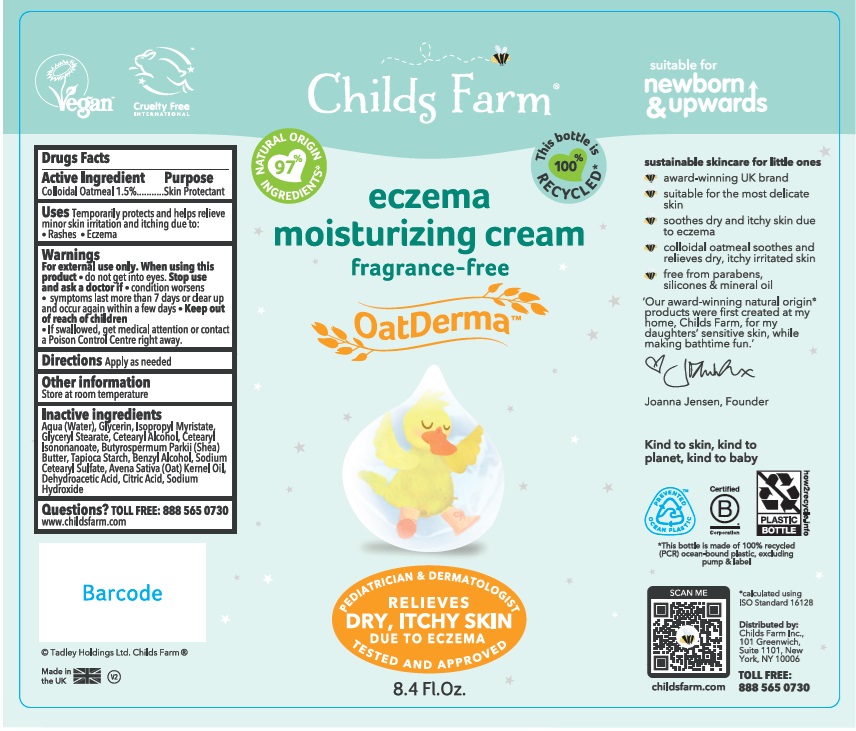 DRUG LABEL: Childs Farm Eczema Moisturizing Cream
NDC: 83244-001 | Form: CREAM
Manufacturer: Childs Farm, Inc.
Category: otc | Type: HUMAN OTC DRUG LABEL
Date: 20241218

ACTIVE INGREDIENTS: OATMEAL 15 mg/1 mL
INACTIVE INGREDIENTS: CETOSTEARYL ALCOHOL; DEHYDROACETIC ACID; SODIUM HYDROXIDE; WATER; GLYCERIN; ISOPROPYL MYRISTATE; GLYCERYL MONOSTEARATE; CETEARYL ISONONANOATE; STARCH, TAPIOCA; SHEA BUTTER; BENZYL ALCOHOL; SODIUM CETOSTEARYL SULFATE; CITRIC ACID MONOHYDRATE; OAT KERNEL OIL

Childs Farm Eczema Moisturizing Cream

Active Ingredient

Colloidal Oatmeal 1.5%

Purpose

Skin Protectant

Uses

Temporarily protects and helps relieve minor skin irritation and itching due to:

- Rashes
- Eczema

Warnings

For external use only.

When using this product

- do not get into eyes.

Stop use and ask a doctor if

- condition worsens
- symptoms last more than 7 days or clear up and occur again within a few days.

Keep out of reach of children

If swallowed, get medical help or contact a Poison Control Centre right away.

Directions

Apply as needed

Other information

Store at room temperature

Inactive ingredients

Aqua (Water), Glycerin, Isopropyl Myristate, Glyceryl Stearate, Cetearyl Alcohol, Cetearyl Isononanoate, Butyrospermum Parkii (Shea) Butter, Tapioca Starch, Benzyl Alcohol, Sodium Cetearyl Sulfate, Avena Sativa (Oat) Kernel Oil, Dehydroacetic Acid, Citric Acid, Sodium Hydroxide

Questions?

TOLL FREE: 888 565 0730

www.childsfarm.com

Company Information

Distributed by:

Childs Farm Inc.,

101 Greenwich, Suite 1101

New York, NY 10006